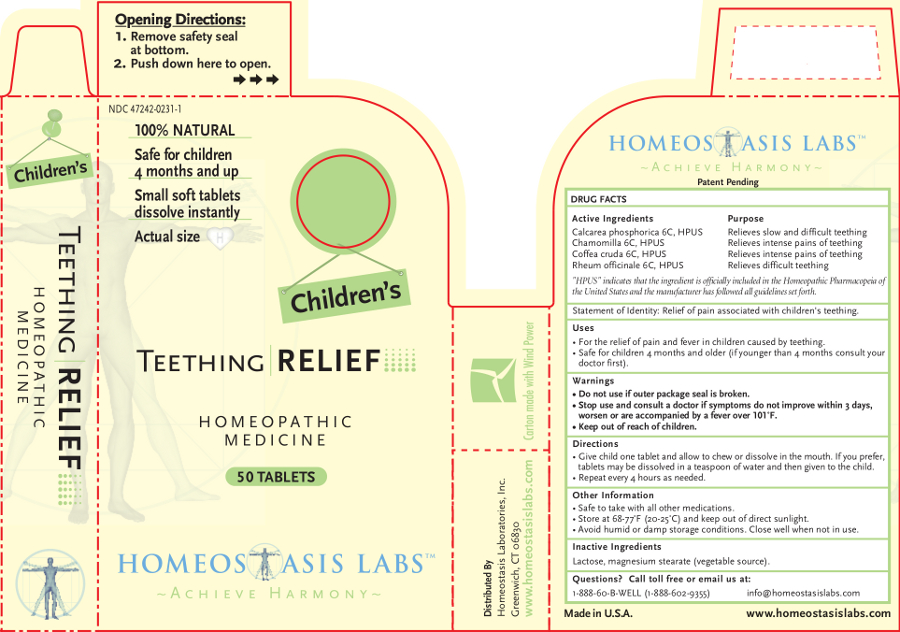 DRUG LABEL: Childrens Teething RELIEF
NDC: 47242-0231 | Form: TABLET, CHEWABLE
Manufacturer: Homeostasis Laboratories, Inc.
Category: homeopathic | Type: HUMAN OTC DRUG LABEL
Date: 20121114

ACTIVE INGREDIENTS: TRIBASIC CALCIUM PHOSPHATE 6 [hp_C]/1 1; MATRICARIA RECUTITA 6 [hp_C]/1 1; ARABICA COFFEE BEAN 6 [hp_C]/1 1; RHEUM OFFICINALE ROOT 6 [hp_C]/1 1
INACTIVE INGREDIENTS: LACTOSE; MAGNESIUM STEARATE

Children's Teething RELIEF

Active Ingredients | Purpose
Calcarea phosphorica 6C, HPUS | Relieves slow and difficult teething
Chamomilla 6C, HPUS | Relieves intense pains of teething
Coffea cruda 6C, HPUS | Relieves intense pains of teething
Rheum officinale 6C, HPUS | Relieves difficult teething

"HPUS" indicates that the ingredient is officially included in the Homeopathic Pharmacopeia of the United States and the manufacturer has followed all guidelines set forth.

Statement of Identity: Relief of pain associated with children's teething.

Uses

For the relief of pain and fever in children caused by teething.

Safe for children 4 months and older (if younger than 4 months consult your doctor first).

Warnings

- Do not use if outer package seal is broken.
- Stop use and consult a doctor if symptoms do not improve within 3 days, worsen or are accompanied by a fever over 101˚F.

- Keep out of reach of children.

Directions

Give child one tablet and allow to chew or dissolve in the mouth. If you prefer, tablets may be dissolved in a teaspoon of water and then given to the child.

Repeat every 4 hours as needed.

Other information

- Safe to take with all other medications.
- Store at 68-77°F (20-25°C) and keep out of direct sunlight.
- Avoid humid or damp storage conditions. Close well when not in use.

Inactive Ingredients

Lactose, magnesium stearate (vegetable source).

Questions? Call toll free or email us at:

1-888-60-B-WELL (1-888-602-9355)

info@homeostasislabs.com